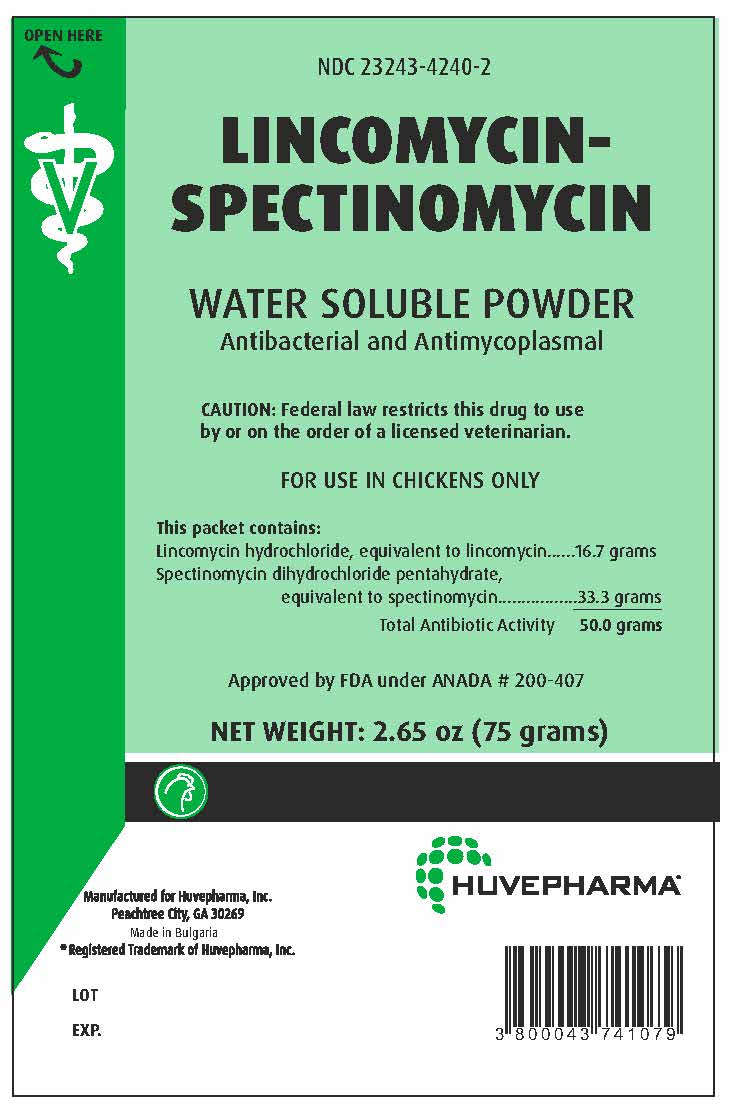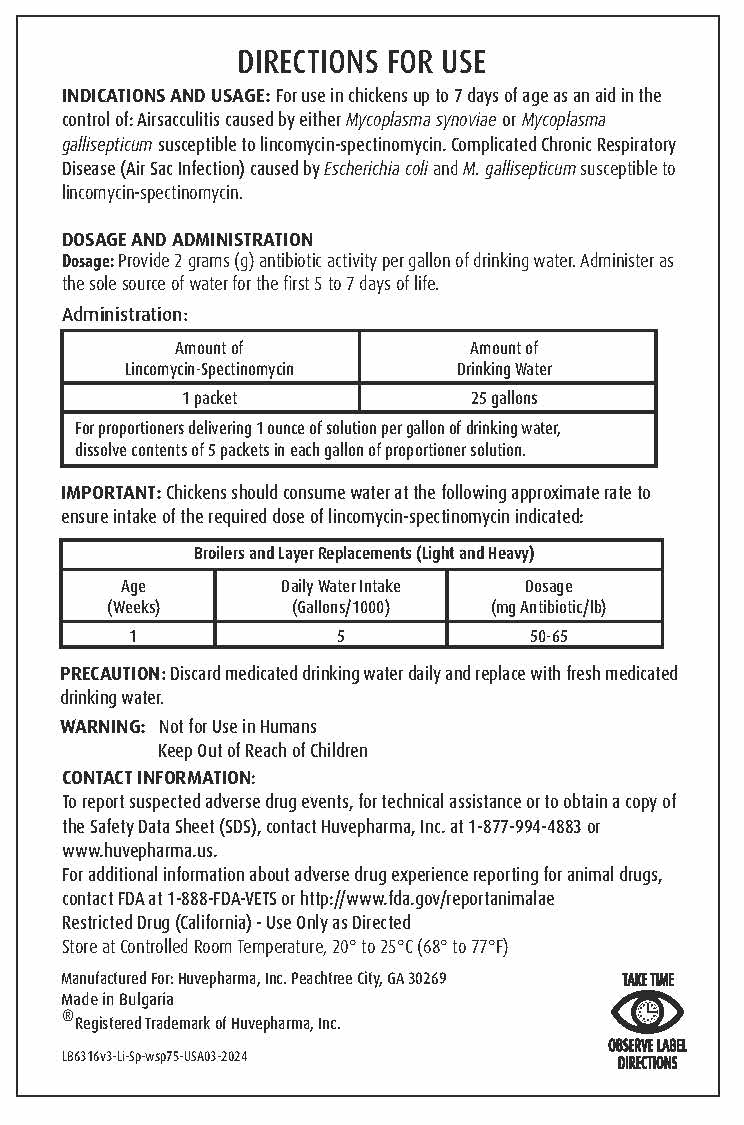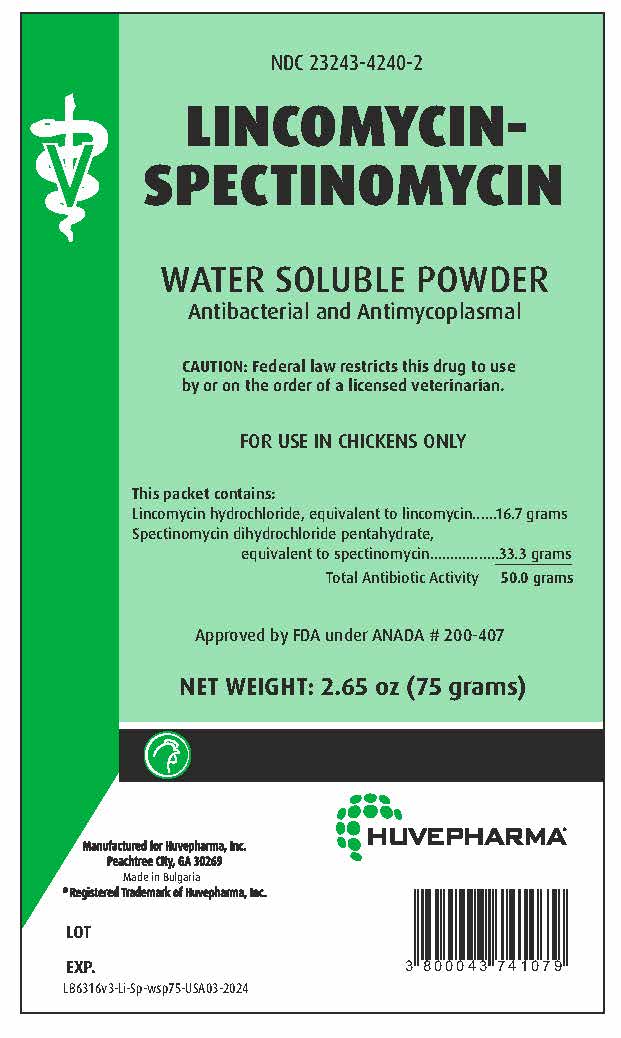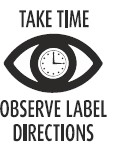 DRUG LABEL: Lincomycin-Spectinomycin
NDC: 23243-4240 | Form: POWDER, FOR SOLUTION
Manufacturer: Huvepharma, Inc
Category: animal | Type: PRESCRIPTION ANIMAL DRUG LABEL
Date: 20250416

ACTIVE INGREDIENTS: LINCOMYCIN HYDROCHLORIDE 16.7 g/75 g; SPECTINOMYCIN HYDROCHLORIDE 33.3 g/75 g
INACTIVE INGREDIENTS: Sucrose

NDC 23243-4240-2

LINCOMYCIN-SPECTINOMYCIN

WATER SOLUBLE POWDER
Antibacterial and Antimycoplasmal

GENERAL PRECAUTIONS

CAUTION: Federal law restricts this drug to
use by or on the order of a licensed veterinarian.

FOR USE IN CHICKENS ONLY

DOSAGE AND ADMINISTRATION

This packet contains:
Lincomycin hydrochloride, equivalent to lincomycin ...... 16.7 grams
Spectinomycin dihydrochloride pentahydrate,
equivalent to spectinomycin.................33.3 grams
Total Antibiotic Activity 50.0 grams Approved by FDA under ANADA # 200-407
NET WEIGHT: 2.65 oz (75 grams)

Manufactured for Huvepharma, Inc.
Peachtree City, Georgia 30269
Made in Bulgaria ® Registered Trademark of Huvepharma, Inc. LOT EXP.

INDICATIONS AND USAGE

DIRECTIONS FOR USE
INDICATIONS AND USAGE: For use in chickens up to 7 days of age as an aid in the control of:
Airsacculitis caused by either Mycoplasma synoviae or Mycoplasma gallisepticum susceptible to lincomycin-spectinomycin.
Complicated Chronic Respiratory Disease (Air Sac Infection) caused by Escherichia coli and M. gallisepticum susceptible
to lincomycin-spectinomycin.

DOSAGE AND ADMINISTRATION
Dosage: Provide 2 grams (g) antibiotic activity per gallon of drinking water. Administer as the sole source of water for the first 5 to 7 days of life.

Administration:

Amount of Lincomycin-Spectinomycin | Amount of Drinking Water
1 packet | 25 gallons
For proportioners delivering 1 ounce of solution per gallon of drinking water,
dissolve contents of 5 packets in each gallon of proportioner solution.

IMPORTANT: Chickens should consume water at the following approximate rate to ensure intake of the required dose of lincomycin-spectinomycin indicated:

Broilers and Layer Replacements (Light and Heavy)
Age (Weeks) | Daily Water Intake (Gallons/1000) | Dosage (mg Antibiotic/lb)
1 | 5 | 50-65

GENERAL PRECAUTIONS

PRECAUTION: Discard medicated drinking water daily and replace with fresh medicated drinking water.

USER SAFETY WARNINGS

WARNING: Not for Use in Humans
Keep Out of Reach of Children

CONTACT INFORMATION:
To report suspected adverse drug events, for technical assistance or to obtain a
copy of the Safety Data Sheet (SDS), contact Huvepharma, Inc. at 1-877-994-4883
or www.huvepharma.us.

For additional information about adverse drug experience reporting for animal drugs,
contact FDA at 1-888-FDA-VETS or http://www.fda.gov/reportanimalae

STORAGE AND HANDLING

Restricted Drug (California) - Use Only as Directed
Store at Controlled Room Temperature, 20° to 25°C (68° to 77°F)

Manufactured For: Huvepharma, Inc. Peachtree City, GA 30269

Made in Bulgaria

® Registered Trademark of Huvepharma, Inc.